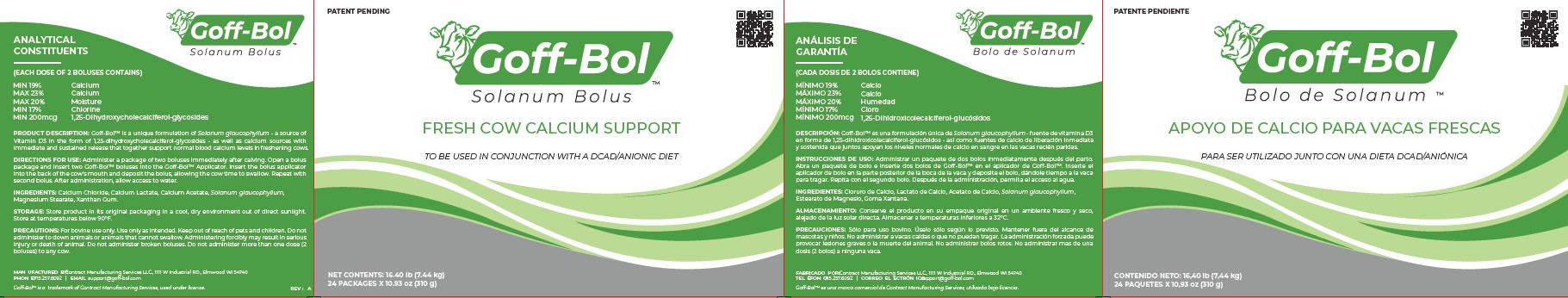 DRUG LABEL: Goff-Bol
NDC: 86158-2084 | Form: TABLET
Manufacturer: Contract Manufacturing Services LLC
Category: animal | Type: OTC ANIMAL DRUG LABEL
Date: 20250709

ACTIVE INGREDIENTS: SOLANUM GLAUCOPHYLLUM WHOLE 8.6 g/310 g; CALCIUM CHLORIDE 110 g/310 g; CALCIUM ACETATE 93.4 g/310 g; CALCIUM LACTATE PENTAHYDRATE 93.4 g/310 g
INACTIVE INGREDIENTS: XANTHAN GUM 0.6 g/310 g; MAGNESIUM STEARATE 4 g/310 g

Goff-Bol™

Product Description

Goff-Bol is a unique formulation of Solanum glaucophyllum - a source of Vitamin D3 in the form of 1,25-Dihydroxycholecalciferol-glycosides - as well as calcium sources with immediate and sustained release that together support normal blood calcium levels in freshening cows.

Directions for Use

Administer a package of two boluses immediately after calving. Open a bolus package and insert two Goff-Bol Max boluses into the Goff-Bol Applicator. Insert the bolus applicator into the back of the cow's mouth and deposit the bolus, allowing the cow time to swallow. Repeat with second bolus. After administration, allow access to water. This product should not be used in conjuction with an anionic/DCAD diet.

Analytical Constituents

Each dose of 2 boluses (310g) contains:

19.0%-23.0% Calcium

200µg 1,25-dihydroxycholecalciferol-glycosides

Active Ingredients

Calcium Chloride, Calcium lactate, Calcium acetate, Solanum glaucophyllum

Inactive Ingredients

Magnesium Stearate, Xanthan Gum

Precautions

For bovine use only. Use only as intended. Keep out of reach of pets and children. Do not administer to down animals or animals that cannot swallow. Administering forcibly may result in serious injury or death of animal. Do not administer broken boluses. Do not administer more than one dose (2 boluses) to any cow.

Principal label image

Goff-Bol Solanum Bolus.

Fresh Cow calcium support

To be used in conjunction with DCAD/Anionic diet